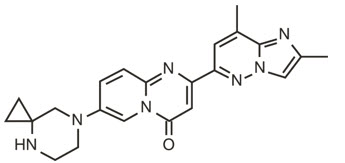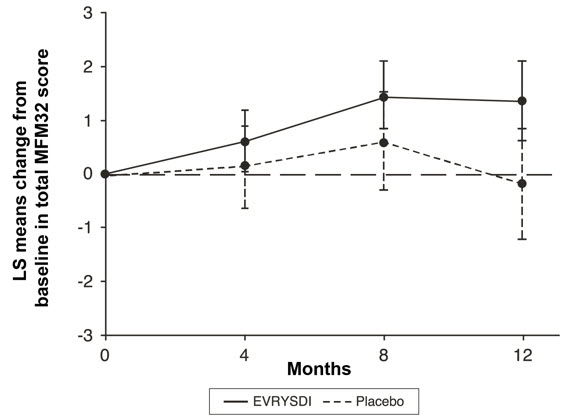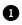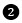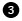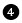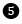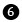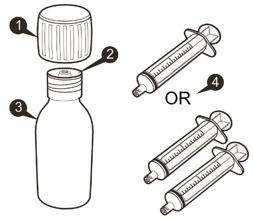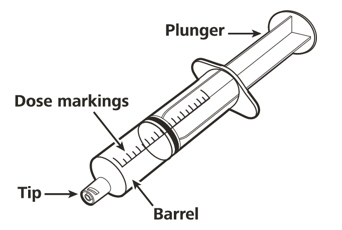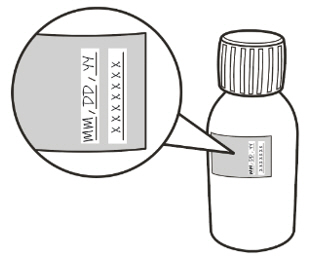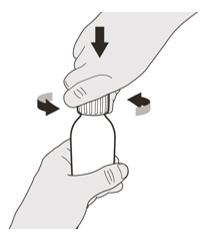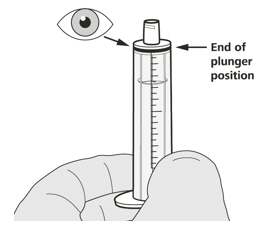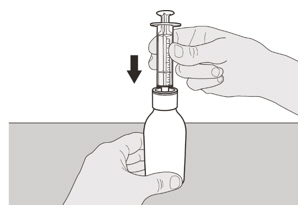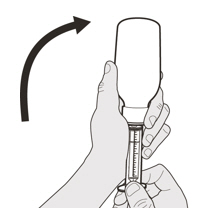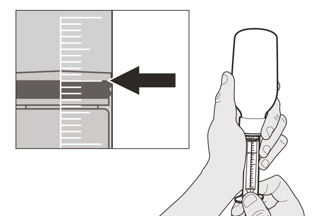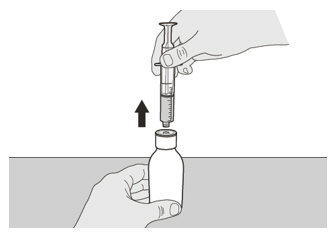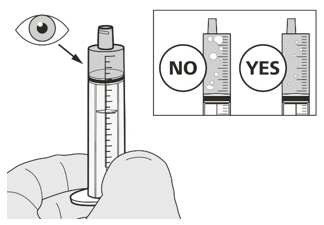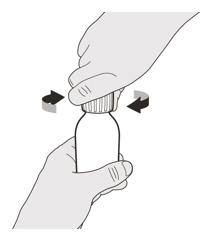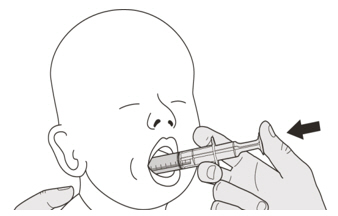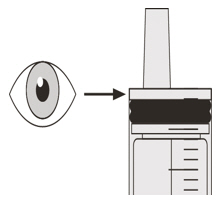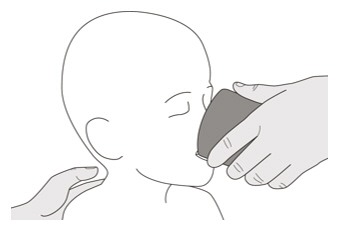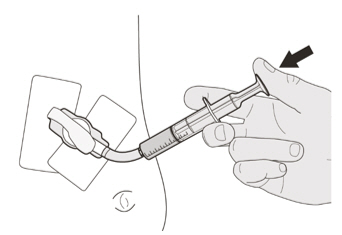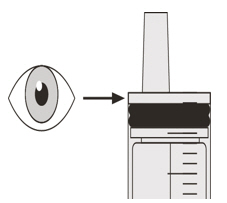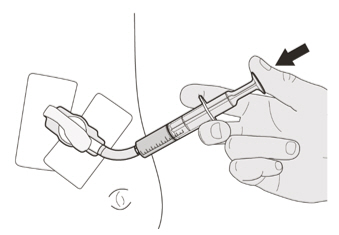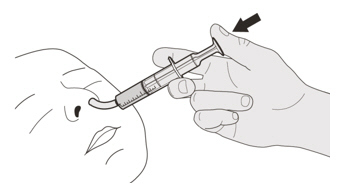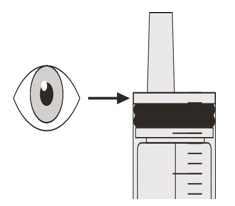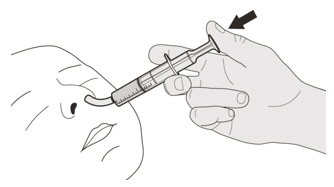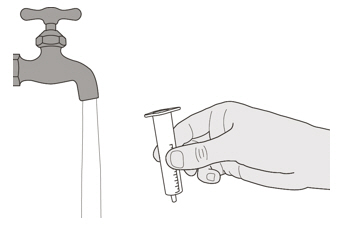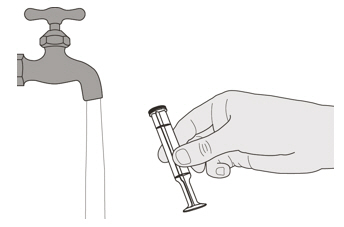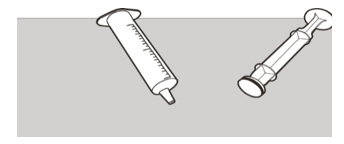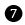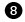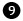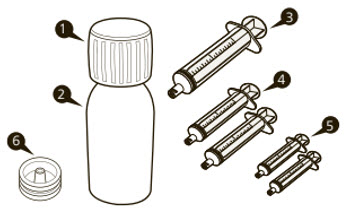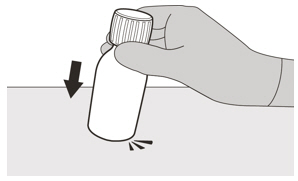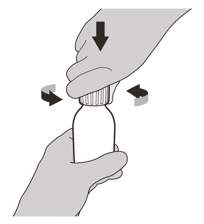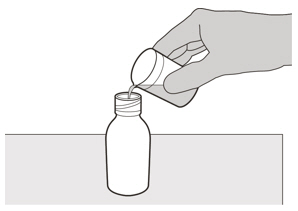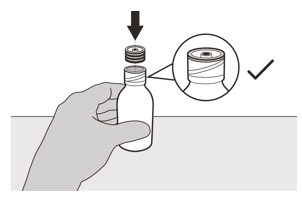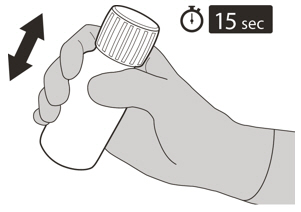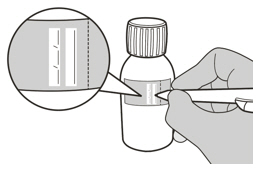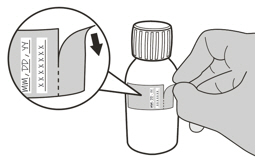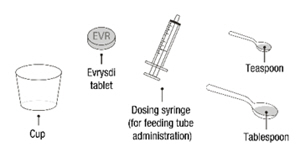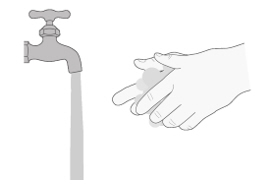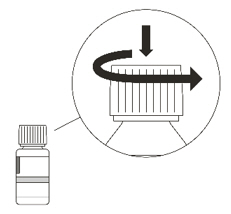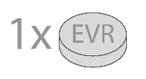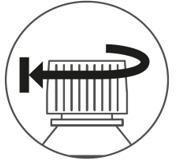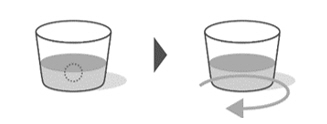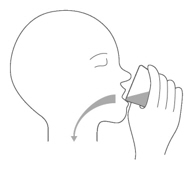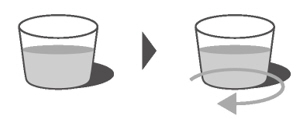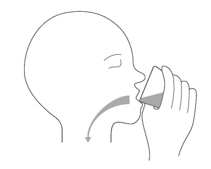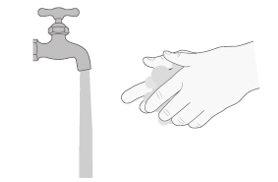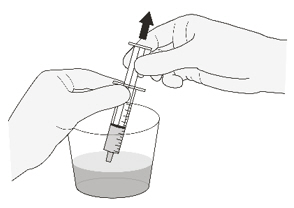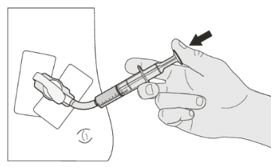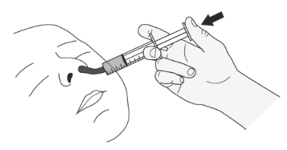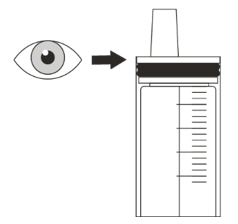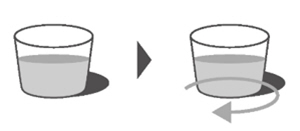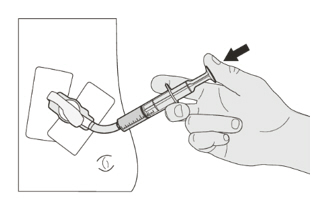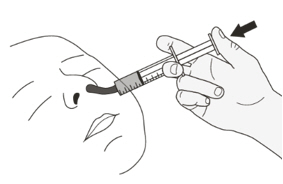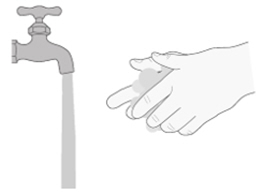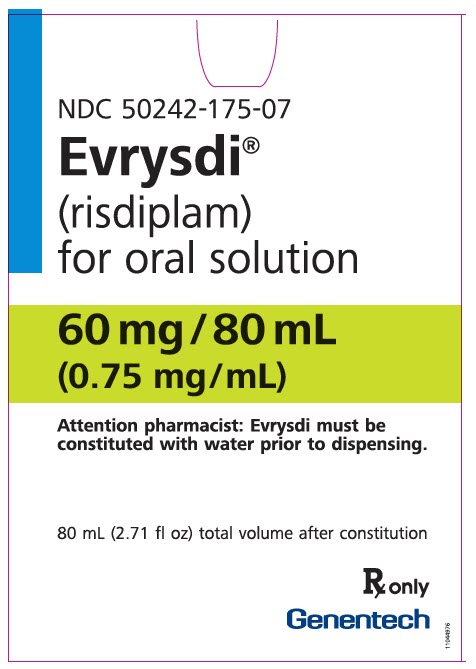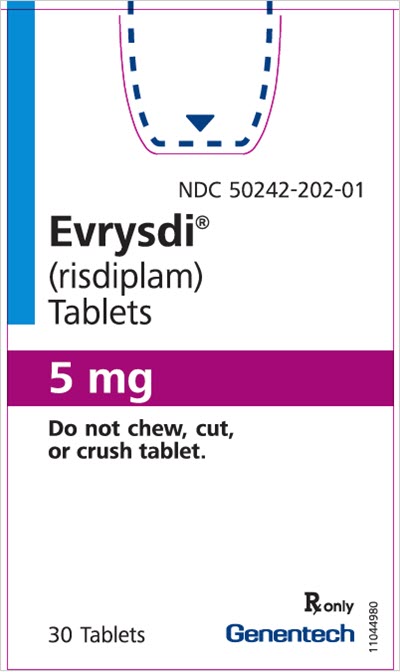 DRUG LABEL: EVRYSDI
NDC: 50242-175 | Form: POWDER, FOR SOLUTION
Manufacturer: Genentech, Inc.
Category: prescription | Type: HUMAN PRESCRIPTION DRUG LABEL
Date: 20260219

ACTIVE INGREDIENTS: RISDIPLAM 0.75 mg/1 mL
INACTIVE INGREDIENTS: MANNITOL 16.81 mg/1 mL; ISOMALT 2.97 mg/1 mL; MALTODEXTRIN 1.88 mg/1 mL; TARTARIC ACID 1.51 mg/1 mL; SODIUM BENZOATE 0.38 mg/1 mL; POLYETHYLENE GLYCOL, UNSPECIFIED 0.25 mg/1 mL; SUCRALOSE 0.2 mg/1 mL; ASCORBIC ACID 0.18 mg/1 mL; EDETATE DISODIUM 0.09 mg/1 mL

HIGHLIGHTS OF PRESCRIBING INFORMATION

These highlights do not include all the information needed to use EVRYSDI safely and effectively. See full prescribing information for EVRYSDI.
EVRYSDI® (risdiplam) for oral solution
EVRYSDI® (risdiplam) tablets, for oral use
Initial U.S. Approval: 2020

RECENT MAJOR CHANGES

Dosage and Administration (2.1, 2.2) | 2/2026

1 INDICATIONS AND USAGE

EVRYSDI is a survival of motor neuron 2 (SMN2) splicing modifier indicated for the treatment of spinal muscular atrophy (SMA) in pediatric and adult patients. (1)

2 DOSAGE AND ADMINISTRATION

- Administer once daily with or without food per the table below (2.1):

Age and Body Weight | Recommended Daily Dosage | Dosage Form
Less than 2 months of age | 0.15 mg/kg | EVRYSDI for Oral Solution
2 months to less than 2 years of age | 0.2 mg/kg | EVRYSDI for Oral Solution
2 years of age and older weighing less than 20 kg | 0.25 mg/kg | EVRYSDI for Oral Solution
2 years of age and older weighing 20 kg or more | 5 mg | EVRYSDI for Oral Solution or EVRYSDI Tablet

- Swallow EVRYSDI tablet whole with water or dispersed in non-chlorinated drinking water (e.g., filtered water). (2.2)
- Administer EVRYSDI for oral solution with the provided oral syringe. (2.2)
- EVRYSDI for oral solution must be constituted by a healthcare provider prior to dispensing. (2.4)
- See Full Prescribing Information for important preparation and administration instructions. (2.2, 2.4)

3 DOSAGE FORMS AND STRENGTHS

- For Oral Solution: 60 mg of risdiplam as a powder for constitution to provide 0.75 mg/mL solution. (3)
- Tablets: 5 mg

4 CONTRAINDICATIONS

None. (4)

6 ADVERSE REACTIONS

The most common adverse reactions in later-onset SMA (incidence at least 10% of patients treated with EVRYSDI and more frequent than control) were fever, diarrhea, and rash. (6.1)

The most common adverse reactions in infantile-onset SMA were similar to those observed in later-onset SMA patients. Additionally, adverse reactions with an incidence of at least 10% were upper respiratory tract infection, lower respiratory tract infection, constipation, vomiting, and cough. (6.1)

To report SUSPECTED ADVERSE REACTIONS, contact Genentech at 1-888-835-2555 or FDA at 1-800-FDA-1088 or www.fda.gov/medwatch.

7 DRUG INTERACTIONS

Avoid coadministration with drugs that are substrates of multidrug and toxin extrusion (MATE) transporters. (7.1)

8 USE IN SPECIFIC POPULATIONS

Pregnancy: Based on animal data, may cause fetal harm. (8.1)

FULL PRESCRIBING INFORMATION

1 INDICATIONS AND USAGE

EVRYSDI is indicated for the treatment of spinal muscular atrophy (SMA) in pediatric and adult patients.

2 DOSAGE AND ADMINISTRATION

2.1 Dosing Information

EVRYSDI is administered orally once daily with or without food at approximately the same time each day. The recommended dosage is determined by age and body weight (see Table 1). EVRYSDI tablets are available for patients prescribed the 5 mg dose.

Table 1 Adult and Pediatric Dosing Regimen by Age and Body Weight
Age and Body Weight | Recommended Daily Dosage | Dosage Form
Less than 2 months of age | 0.15 mg/kg | EVRYSDI for Oral Solution
2 months to less than 2 years of age | 0.2 mg/kg | EVRYSDI for Oral Solution
2 years of age and older weighing less than 20 kg | 0.25 mg/kg | EVRYSDI for Oral Solution
2 years of age and older weighing 20 kg or more | 5 mg | EVRYSDI for Oral Solution or EVRYSDI Tablet

2.2 Important Administration Instructions

It is recommended that a healthcare provider discuss with the patient or caregiver how to prepare the prescribed daily dose prior to administration of the first dose [see Instructions for Use for EVRYSDI for Oral Solution and EVRYSDI Tablets and Patient Information].

EVRYSDI for Oral Solution

In infants who are breastfed, EVRYSDI for oral solution can be administered before or after breastfeeding. EVRYSDI cannot be mixed with formula or milk.

Instruct patients or caregivers to administer the dose using the reusable oral syringe provided.

EVRYSDI for oral solution must be taken immediately after it is drawn up into the oral syringe. If EVRYSDI is not taken within 5 minutes, EVRYSDI should be discarded from the oral syringe, and a new dose should be prepared.

Instruct patients to drink water after taking EVRYSDI for oral solution to ensure the drug has been completely swallowed.

EVRYSDI for oral solution can be administered via a nasogastric or gastrostomy tube. The tube should be flushed with water after delivering EVRYSDI for oral solution [see Instructions for Use].

EVRYSDI Tablets

Swallow EVRYSDI tablets whole with water. Do not chew, cut, or crush the tablets.

Alternatively, the EVRYSDI tablet can also be dispersed in one teaspoon (5 mL) of room temperature non-chlorinated drinking water (e.g., filtered water). EVRYSDI tablets must not be dispersed in any liquid other than non-chlorinated drinking water. Do not expose the prepared dispersion to sunlight. Swirl the small cup gently for up to 3 minutes until fully mixed (though some particles will remain). Administer the dispersed tablet immediately. To ensure no particles are left in the small cup, refill it with at least one tablespoon (15 mL) of non-chlorinated drinking water, swirl, and administer immediately again.

EVRYSDI must be taken immediately after it is dispersed in non-chlorinated drinking water. Discard the prepared dispersion if it is not used within 10 minutes of adding non-chlorinated drinking water.

The dispersed EVRYSDI tablet can be administered via a nasogastric or gastrostomy tube that is 8 French or higher. Flush the tube with the non-chlorinated drinking water [at least one tablespoon (15 mL)] used to rinse the dispersion cup [see Instructions for Use].

2.3 Missed Dose

If a dose of EVRYSDI is missed, EVRYSDI should be administered as soon as possible if still within 6 hours of the missed dose, and the usual dosing schedule can be resumed on the next day. Otherwise, the missed dose should be skipped, and the next dose should be taken at the regularly scheduled time on the next day.

If a dose is not fully swallowed or vomiting occurs after taking a dose of EVRYSDI, another dose should not be administered to make up for the lost dose. The patient should wait until the next day to take the next dose at the regularly scheduled time.

2.4 Preparation of Powder for Oral Solution by Healthcare Provider

EVRYSDI powder must be constituted to the oral solution by a pharmacist or other healthcare provider prior to dispensing to the patient.

Preparation of the EVRYSDI Oral Solution 0.75 mg/mL

The EVRYSDI "Instructions for Constitution" booklet contains more detailed instructions on the preparation of the oral solution [see Instructions for Constitution].

Caution should be exercised when handling EVRYSDI powder for oral solution. Avoid inhalation and direct contact with skin or mucous membranes with the dry powder and the constituted solution. If such contact occurs, wash thoroughly with soap and water; rinse eyes with water. Wear disposable gloves during the preparation and cleanup procedure.

1. Gently tap the bottom of the closed glass bottle to loosen the powder.
2. Remove the cap. Do not throw away the cap.
3. Carefully pour 79 mL of purified water into the EVRYSDI bottle to yield the 0.75 mg/mL oral solution. Do not mix EVRYSDI with formula or milk.
4. Insert the press-in bottle adapter into the bottle opening by pushing it down against the bottle lip. Ensure it is completely pressed against the bottle lip.
5. Re-cap the bottle tightly and shake well for 15 seconds. Wait for 10 minutes. You should have obtained a clear solution. If not, shake well again for another 15 seconds or until you have obtained a clear solution.
6. Write the date of expiration of the constituted oral solution (calculated as 64 days after constitution) and the lot number on the bottle label. Peel off the part of the bottle label that has the expiration date of the powder.
7. Put the bottle back in its original carton.
8. Select the appropriate oral syringes (1 mL, 6 mL, or 12 mL) based on the patient's dosage and remove the other oral syringes from the carton.
9. Dispense with the "Instructions for Use" and FDA-approved patient labeling. Alert patients to read the important handling information described in the Instructions for Use.

Storage

Keep the constituted oral solution of EVRYSDI in the original amber bottle to protect from light. Store in a refrigerator at 2°C to 8°C (36°F to 46°F). Do not freeze. Discard any unused portion 64 days after constitution. Keep the bottle in an upright position with the cap tightly closed. If refrigeration is not available, EVRYSDI can be kept at room temperature up to 40°C (up to 104°F) for a combined total of 5 days. EVRYSDI can be removed from, and returned to, a refrigerator. The total combined time out of refrigeration should not exceed 5 days.

3 DOSAGE FORMS AND STRENGTHS

EVRYSDI for oral solution: 60 mg as a light yellow, pale yellow, yellow, greyish yellow, greenish yellow, or light green powder for constitution. Following constitution, the volume of the greenish yellow to yellow solution is 80 mL, providing 60 mg/80 mL (0.75 mg/mL) risdiplam.

EVRYSDI tablet: 5 mg as a pale yellow film-coated tablet, round and curved, with EVR debossed on one side.

4 CONTRAINDICATIONS

None.

6 ADVERSE REACTIONS

6.1 Clinical Trials Experience

Because clinical trials are conducted under widely varying conditions, adverse reaction rates observed in the clinical trials of a drug cannot be directly compared to rates in clinical trials of another drug and may not reflect the rates observed in practice.

In clinical trials including patients with infantile-onset SMA, later-onset SMA, and pre-symptomatic SMA, a total of 491 patients (51% female, 74% Caucasian) were exposed to EVRYSDI for up to a median duration of 48.1 months (range: 0.6 to 63.4 months), with 231 patients receiving treatment for more than 24 months. At the time of first EVRYSDI dose, 90 (18%) patients were 18 years and older, 119 (24%) were 12 years to less than 18 years, 189 (39%) were 2 years to less than 12 years, 67 (14%) 2 months to less than 2 years, and 26 (5%) were less than 2 months.

Clinical Trial in Later-Onset SMA

The safety of EVRYSDI for later-onset SMA is based on data from a randomized, double-blinded, placebo-controlled study (Study 2 Part 2) in patients with SMA Type 2 or 3 (n = 180) [see Clinical Studies (14.2)]. The patient population in Study 2 Part 2 ranged in age from 2 to 25 years at the time of the first dose.

The most common adverse reactions (reported in at least 10% of patients treated with EVRYSDI and at an incidence greater than on placebo) in Study 2 Part 2 were fever, diarrhea, and rash. Table 2 lists the adverse reactions that occurred in at least 5% of patients treated with EVRYSDI and at an incidence ≥ 5% greater than on placebo in Study 2 Part 2.

Table 2 Adverse Reactions Reported in ≥ 5% of Patients Treated with EVRYSDI and with an Incidence ≥ 5% Greater Than on Placebo in Study 2 Part 2
Adverse Reaction | EVRYSDI (N = 120) % | Placebo (N = 60) %
Fever [Includes pyrexia and hyperpyrexia.] | 22 | 17
Diarrhea | 17 | 8
Rash [Includes rash, erythema, rash maculo-papular, rash erythematous, rash papular, dermatitis allergic, and folliculitis.] | 17 | 2
Mouth and aphthous ulcers | 7 | 0
Arthralgia | 5 | 0
Urinary tract infection [Includes urinary tract infection and cystitis.] | 5 | 0

Clinical Trial in Infantile-Onset SMA

The safety of EVRYSDI therapy for infantile-onset SMA is based on data from an open-label study in 62 patients (Study 1) [see Clinical Studies (14.1)]. The patient population ranged in age from 2 to 7 months at the time of the first EVRYSDI dose (weight range: 4.1 to 10.6 kg).

The most frequent adverse reactions reported in infantile-onset SMA patients treated with EVRYSDI in Study 1 were similar to those observed in later-onset SMA patients in Study 2. Additionally, the following adverse reactions reported in ≥ 10% of patients were: upper respiratory tract infection (including nasopharyngitis, rhinitis), lower respiratory tract infection (including pneumonia, bronchitis), constipation, vomiting, and cough.

Clinical Trial in Pre-Symptomatic SMA

The safety of EVRYSDI therapy for pre-symptomatic SMA is based on data from an open-label, single-arm study in 26 patients (Study 3) [see Clinical Studies (14.3)]. The patient population ranged in age from 16 to 41 days at the time of the first dose (weight range: 3.1 to 5.7 kg). The safety profile of EVRYSDI in pre-symptomatic patients in Study 3 is consistent with the safety profile for symptomatic SMA patients treated with EVRYSDI in clinical trials.

7 DRUG INTERACTIONS

7.1 Effect of EVRYSDI on Substrates of Multidrug and Toxin Extrusion (MATE) Protein Transporters

Based on in vitro data, EVRYSDI may increase plasma concentrations of drugs eliminated via MATE1 or MATE2-K [see Clinical Pharmacology (12.3)], such as metformin. Avoid coadministration of EVRYSDI with MATE substrates. If coadministration cannot be avoided, monitor for drug-related toxicities and consider dosage reduction of the coadministered drug (based on the labeling of that drug) if needed.

8 USE IN SPECIFIC POPULATIONS

8.1 Pregnancy

Pregnancy Exposure Registry

There is a pregnancy exposure registry that monitors pregnancy and fetal/neonatal/infant outcomes in women exposed to EVRYSDI during pregnancy. Physicians are encouraged to register patients and pregnant women are encouraged to register themselves by calling 1-833-760-1098 or visiting https://www.evrysdipregnancyregistry.com.

Risk Summary

There are no adequate data on the developmental risk associated with the use of EVRYSDI in pregnant women. In animal studies, administration of risdiplam during pregnancy or throughout pregnancy and lactation resulted in adverse effects on development (embryofetal mortality, malformations, decreased fetal body weights, and reproductive impairment in offspring) at or above clinically relevant drug exposures [see Data].

The estimated background risk of major birth defects and miscarriage for the indicated populations is unknown. In the U.S. general population, the estimated background risk of major birth defect and miscarriage in clinically recognized pregnancies is 2% to 4% and 15% to 20%, respectively. Based on animal data, advise pregnant women of the potential risk to the fetus.

Data

Animal Data

Oral administration of risdiplam (0, 1, 3, or 7.5 mg/kg/day) to pregnant rats throughout organogenesis resulted in decreased fetal body weights and increased incidences of fetal structural variations at the highest dose tested, which was not associated with maternal toxicity. The no-effect level for adverse effects on embryofetal development (3 mg/kg/day) was associated with maternal plasma exposure (AUC) approximately 2 times that in humans at the maximum recommended human dose (MRHD) of 5 mg.

Oral administration of risdiplam (0, 1, 4, or 12 mg/kg/day) to pregnant rabbits throughout organogenesis resulted in embryofetal mortality, fetal malformations (hydrocephaly), and structural variations at the highest dose tested, which was associated with maternal toxicity. The no-effect dose for adverse effects on embryofetal development (4 mg/kg/day) was associated with maternal plasma exposure (AUC) approximately 4 times that in humans at the MRHD.

When risdiplam (0, 0.75, 1.5, or 3 mg/kg/day) was orally administered to rats throughout pregnancy and lactation, gestation was prolonged in the dams, and delayed sexual maturation (vaginal opening) and impaired reproductive function (decreased numbers of corpora lutea, implantation sites, and live embryos) were observed in female offspring at the highest dose. The no-effect dose for adverse effects on pre- and postnatal development in rats (1.5 mg/kg/day) was associated with maternal plasma exposure (AUC) similar to that in humans at the MRHD.

8.2 Lactation

Risk Summary

There are no data on the presence of risdiplam in human milk, the effects on the breastfed infant, or the effects on milk production. Risdiplam was excreted in the milk of lactating rats orally administered risdiplam.

The developmental and health benefits of breastfeeding should be considered along with the mother's clinical need for EVRYSDI and any potential adverse effects on the breastfed infant from EVRYSDI or from the underlying maternal condition.

8.3 Females and Males of Reproductive Potential

Studies of risdiplam in juvenile and adult rats and in monkeys demonstrated adverse effects on the reproductive organs, including germ cells, in males at clinically relevant plasma exposures [see Use in Specific Populations (8.4) and Nonclinical Toxicology (13.1)].

Pregnancy Testing

Pregnancy testing is recommended for females of reproductive potential prior to initiating EVRYSDI [see Use in Specific Populations (8.1)].

Contraception

EVRYSDI may cause embryofetal harm when administered to a pregnant woman [see Use in Specific Populations (8.1)].

Female Patients

Advise female patients of reproductive potential to use effective contraception during treatment with EVRYSDI and for at least 1 month after her last dose.

Infertility

Male Patients

Male fertility may be compromised by treatment with EVRYSDI [see Nonclinical Toxicology (13.1)].

Counsel male patients of reproductive potential receiving EVRYSDI about the potential effects on fertility. Male patients may consider sperm preservation prior to treatment.

8.4 Pediatric Use

The safety and effectiveness of EVRYSDI in pediatric patients (neonates and older) have been established. Use of EVRYSDI for SMA is supported by evidence from adequate and well-controlled studies of EVRYSDI in patients 2 months of age and older with SMA. Use of EVRYSDI for SMA in patients 2 months of age and younger is supported by pharmacokinetic and safety data from pediatric patients 16 days and older, and pharmacokinetic modeling and simulation to identify the dosing regimen [see Clinical Pharmacology (12.3) and Clinical Studies (14)].

Juvenile Animal Toxicity Data

Oral administration of risdiplam (0, 0.75, 1.5, 2.5 mg/kg/day) to young rats from postnatal day (PND) 4 through PND 31 resulted in decreased growth (body weight, tibia length) and delayed sexual maturation in males at the mid and high dose. The skeletal and body weight deficits persisted after cessation of dosing. Ophthalmic changes consisting of vacuoles in the anterior vitreous were seen at the high dose. Decreases in absolute B lymphocyte counts were observed at all doses after cessation of dosing. Decreases in testis and epididymis weights, which correlated with degeneration of the seminiferous epithelium in the testis, occurred at the mid and high doses; the histopathology findings were reversible, but organ weight persisted after cessation of dosing. Impaired female reproductive performance (decreased mating index, fertility index, and conception rate) was observed at the high dose. A no-effect dose for adverse developmental effects on preweaning rats was not identified. The lowest dose tested (0.75 mg/kg/day) was associated with plasma exposures (AUC) lower than that in humans at the maximum recommended human dose (MRHD) of 5 mg/day.

Oral administration of risdiplam (0, 1, 3, or 7.5 mg/kg/day) to young rats from PND 22 through PND 112 produced a marked increase in micronuclei in the bone marrow, male reproductive organ histopathology (degeneration/necrosis of the seminiferous tubule epithelium, oligo/aspermia in the epididymis, spermatic granulomas), and adverse effects on sperm parameters (decreased sperm concentration and motility, increased sperm morphology abnormalities) at the highest dose tested. Increases in T lymphocytes (total, helper, and cytotoxic) were observed at the mid and high doses. The reproductive and immune effects persisted after cessation of dosing. The no-effect dose (1 mg/kg/day) for adverse effects on postweaning juvenile rats was associated with plasma exposures (AUC) lower than that in humans at the MRHD.

8.5 Geriatric Use

Clinical studies of EVRYSDI did not include patients aged 65 years and older to determine whether they respond differently from younger adult patients.

11 DESCRIPTION

EVRYSDI for oral solution and EVRYSDI tablets for oral use contain risdiplam, which is a survival of motor neuron 2 (SMN2)-directed RNA splicing modifier.

The chemical name of risdiplam is 7-(4,7-diazaspiro[2.5]octan-7-yl)-2-(2,8 dimethylimidazo[1,2-b]pyridazin-6-yl)pyrido-4H-[1,2-a]pyrimidin-4-one. Risdiplam has a molecular weight of 401.46 g/mol. Risdiplam demonstrates pH-dependent aqueous solubility; the greatest solubility is at low pH, and solubility decreases with increasing pH. Risdiplam has a pKa1 of 3.78 (base) and pKa2 of 6.62 (base).

The molecular formula of risdiplam is C22H23N7O and the chemical structure is shown below.

EVRYSDI for oral solution is supplied as a powder in an amber glass bottle. Each bottle contains 60 mg of risdiplam. The inactive ingredients of EVRYSDI are: ascorbic acid, disodium edetate dihydrate, isomalt, mannitol, polyethylene glycol 6000, sodium benzoate, strawberry flavor, sucralose, and tartaric acid.

The powder is constituted with purified water to yield 60 mg/80 mL (0.75 mg/mL) of risdiplam after constitution [see Dosage and Administration (2.4)].

Each EVRYSDI tablet contains 5 mg of risdiplam. The inactive ingredients of EVRYSDI tablet are colloidal silicon dioxide, crospovidone, mannitol, microcrystalline cellulose, polyethylene glycol 3350, polyvinyl alcohol, sodium stearyl fumarate, strawberry flavor, talc, tartaric acid, titanium dioxide, and yellow iron oxide.

12 CLINICAL PHARMACOLOGY

12.1 Mechanism of Action

Risdiplam is a survival of motor neuron 2 (SMN2) splicing modifier designed to treat patients with spinal muscular atrophy (SMA) caused by mutations in chromosome 5q that lead to SMN protein deficiency. Using in vitro assays and studies in transgenic animal models of SMA, risdiplam was shown to increase exon 7 inclusion in SMN2 messenger ribonucleic acid (mRNA) transcripts and production of full-length SMN protein in the brain.

In vitro and in vivo data indicate that risdiplam may cause alternative splicing of additional genes, including FOXM1 and MADD. FOXM1 and MADD are thought to be involved in cell cycle regulation and apoptosis, respectively, and have been identified as possible contributors to adverse effects seen in animals.

12.2 Pharmacodynamics

In clinical trials for infantile-onset SMA and later-onset SMA patients, EVRYSDI led to an increase in SMN protein with a greater than 2-fold median change from baseline within 4 weeks of treatment initiation across all SMA types studied. The increase was sustained throughout the treatment period (of at least 24 months).

Cardiac Electrophysiology

At the maximum recommended dose, clinically significant QTc interval prolongation was not observed.

12.3 Pharmacokinetics

Pharmacokinetics of EVRYSDI have been characterized in healthy adult subjects and in patients with SMA.

After administration of EVRYSDI as an oral solution, pharmacokinetics of risdiplam were approximately linear between 0.6 and 18 mg in a single-ascending-dose study in healthy adult subjects, and between 0.02 and 0.25 mg/kg once daily in a multiple-ascending-dose study in patients with SMA. Following once-daily oral administration of risdiplam in healthy subjects, approximately 3-fold accumulation of peak plasma concentrations (Cmax) and area under the plasma concentration-time curve (AUC0-24h) was observed. Risdiplam exposures reach steady state 7 to 14 days after once daily administration. EVRYSDI tablet (swallowed whole or dispersed in water) demonstrated comparable bioavailability to EVRYSDI for oral solution in adult healthy volunteers under fasted and fed states.

Absorption

Following oral administration of risdiplam in fasted state, the median time to reach maximum plasma concentration (Tmax) was 3.26 to 4 hours. The Tmax was delayed by up to1 hour in fed state compared to that under fasted state.

Effect of Food

Food (high-fat, high calorie breakfast) had no relevant effect on the exposure of risdiplam. In the clinical efficacy studies (Study 1 and Study 2), risdiplam was administered with a morning meal or after breastfeeding.

Distribution

The apparent volume of distribution at steady state is 190.4 L for a 31.3 kg patient.

Risdiplam is predominantly bound to serum albumin, without any binding to alpha-1 acid glycoprotein, with a free fraction of 11%.

Elimination

The apparent clearance (CL/F) of risdiplam is 2.45 L/h for a 31.3 kg patient.

The terminal elimination half-life of risdiplam was approximately 50 hours in healthy adults.

Metabolism

Risdiplam is primarily metabolized by flavin monooxygenase 1 and 3 (FMO1 and FMO3) and also by CYPs 1A1, 2J2, 3A4, and 3A7.

Parent drug was the major component found in plasma, accounting for 83% of drug-related material in circulation. The pharmacologically-inactive metabolite M1 was identified as the major circulating metabolite.

Excretion

Following a dose of 18 mg, approximately 53% of the dose (14% unchanged risdiplam) was excreted in the feces and 28% in urine (8% unchanged risdiplam).

Specific Populations

There were no clinically significant differences in the pharmacokinetics of EVRYSDI based on race or gender. Renal impairment is not expected to alter the exposures to risdiplam.

The impact of geriatric age on the pharmacokinetics of EVRYSDI has not been studied.

Hepatic Impairment

The pharmacokinetics and safety of risdiplam have been studied in subjects with mild or moderate hepatic impairment (as defined by Child-Pugh class A and B, respectively, n = 8 each) compared to subjects with normal hepatic function (n = 10). Following the administration of 5 mg EVRYSDI, the AUCinf and Cmax of risdiplam were approximately 20% and 5% lower, respectively, in subjects with mild hepatic impairment and were approximately 8% and 20% higher, respectively, in subjects with moderate hepatic impairment, versus matched healthy control subjects. The magnitude of these changes is not considered to be clinically meaningful. The pharmacokinetics and safety in patients with severe hepatic impairment (Child-Pugh class C) have not been studied.

Pediatric Patients

Body weight and age were found to have significant effect on the pharmacokinetics of risdiplam. The estimated exposure (mean AUC0-24h) in pre-symptomatic infants at the age of 1 to 2 months was 2090 ng.h/mL at the recommended dose of 0.15 mg/kg once daily. The estimated exposure for infantile-onset SMA patients (age 2 to 7 months at enrollment) at the recommended dose of 0.2 mg/kg once daily was 1930 ng.h/mL. The estimated exposure for later-onset SMA patients (2 to 25 years old at enrollment) at the recommended dose was 2070 ng.h/mL (0.25 mg/kg once daily for patients with a body weight < 20 kg and 5 mg once daily for patients with a body weight ≥ 20 kg).

No data on risdiplam pharmacokinetics are available in patients less than 16 days of age [see Use in Specific Populations (8.4)].

Drug Interaction Studies

Effect of Other Drugs on EVRYSDI

Coadministration of 200 mg itraconazole (a strong CYP3A inhibitor) twice daily with a single 6 mg oral dose of risdiplam did not have a clinically relevant effect on the pharmacokinetics of risdiplam (11% increase in AUC and 9% decrease in Cmax).

Risdiplam is a weak substrate of human MDR-1 and breast cancer resistant protein (BCRP) transporters in vitro. Human MDR-1 or BCRP inhibitors are not expected to result in a clinically significant increase of risdiplam concentrations.

The effect of omeprazole (an acid-reducing agent/proton pump inhibitor) on risdiplam pharmacokinetics was investigated in healthy subjects. No clinically significant difference was observed in the pharmacokinetics of risdiplam administered as a tablet when used concomitantly with omeprazole. Based on these results, no clinically significant differences are expected with other acid-reducing agents, including H2-receptor antagonists and antacids.

Effect of EVRYSDI on Other Drugs

Risdiplam and its major circulating metabolite M1 did not induce CYP1A2, 2B6, 2C8, 2C9, 2C19, or 3A4 in vitro. Risdiplam and M1 did not inhibit (reversible or time-dependent inhibition) any of the CYP enzymes tested (CYP1A2, 2B6, 2C8, 2C9, 2C19, 2D6), with the exception of CYP3A in vitro.

EVRYSDI is a weak inhibitor of CYP3A. In healthy adult subjects, administration of EVRYSDI once daily for 2 weeks slightly increased the exposure of midazolam, a sensitive CYP3A substrate (AUC 11%; Cmax 16%); this increase is not considered clinically relevant. Based on physiologically-based pharmacokinetic (PBPK) modeling, a similar increase is expected in children and infants as young as 2 months of age.

In vitro studies have shown that risdiplam and its major metabolite are not significant inhibitors of human MDR1, organic anion-transporting polypeptide (OATP) 1B1, OATP1B3, organic anion transporter 1 and 3 (OAT 1 and 3) transporters, and human organic cation transporter 2 (OCT2), at clinically relevant concentrations. Risdiplam and its metabolite are, however, in vitro inhibitors of the multidrug and toxin extrusion (MATE) 1 and MATE2-K transporters [see Drug Interactions (7.1)].

13 NONCLINICAL TOXICOLOGY

13.1 Carcinogenesis, Mutagenesis, Impairment of Fertility

Carcinogenesis

Risdiplam was not carcinogenic in Tg.rasH2 mice when administered at oral doses of up to 9 mg/kg/day for 26 weeks.

In a 2-year carcinogenicity study in rats, oral administration of risdiplam (0, 0.3, 1, or 3 mg/kg/day) resulted in increased incidences of preputial gland squamous cell carcinomas in males and combined thyroid follicular cell adenomas and carcinomas in females at the highest dose tested. The higher dose not associated with an increase in tumors (1 mg/kg/day) was associated with plasma drug exposures (AUC) similar to that in humans at the maximum recommended human dose (MRHD) of 5 mg/day.

Mutagenesis

Risdiplam was negative in an in vitro Ames assay. In an in vivo combined bone marrow micronucleus and comet assay in rat, risdiplam was clastogenic, as evidenced by an increase in micronuclei in bone marrow, but was negative in the comet assay. A pronounced increase in bone marrow micronuclei was also observed in toxicity studies in adult and juvenile rats [see Use in Specific Populations (8.4)].

Impairment of Fertility

Oral administration of risdiplam to rats for 4 (0, 1, 3, or 9 mg/kg/day) or 26 (0, 1, 3, or 7.5 mg/kg/day) weeks resulted in histopathological effects in the testis (degenerated spermatocytes, degeneration/atrophy of the seminiferous tubules) and epididymis (degeneration/necrosis of ductular epithelium) at the mid and/or high doses. At the high dose in the 26-week study, the testicular lesions persisted to the end of the recovery period, which corresponds, in rat, to approximately one spermatogenic cycle. The no-effect dose for adverse reproductive system effects in adult male rats (1 mg/kg/day) was associated with plasma drug exposures (AUC) similar to that in humans at the maximum recommended human dose (MRHD) of 5 mg/day.

Adverse effects of risdiplam on the testis could not be fully evaluated in the monkey because the majority of monkeys tested were sexually immature. However, oral administration of risdiplam (0, 2, 4, or 6 mg/kg/day) for 2 weeks resulted in histopathological changes in the testis (increases in multinucleate cells, germ cell degeneration) at the highest dose. At the no-effect dose for testicular toxicity in monkeys, plasma exposures were approximately 3 times that in humans at the MRHD.

Oral administration of risdiplam to postweaning juvenile rats resulted in male reproductive toxicity (degeneration/necrosis of the testis seminiferous epithelium with associated oligo/aspermia in the epididymis and abnormal sperm parameters). The no-effect dose for adverse reproductive effects in postweaning male juvenile rats was associated with plasma exposures approximately 4 times that in humans at the MRHD [see Use in Specific Populations (8.4)].

13.2 Animal Toxicology and/or Pharmacology

Retinal toxicity

Risdiplam-induced functional and structural retinal abnormalities were seen in animal studies. In a 39-week toxicity study in monkeys, oral administration of risdiplam (0, 1.5, 3, or 7.5/5 mg/kg/day; high dose lowered after 4 weeks) produced functional abnormalities on the electroretinogram (ERG) in all mid- and high-dose animals at the earliest examination time (Week 20). These findings were associated with retinal degeneration, detected by optical coherence tomography (OCT), on Week 22, the first examination time. The retinal degeneration, with peripheral photoreceptor loss, was irreversible. A no-effect dose for the retinal findings (1.5 mg/kg/day) was associated with plasma exposures (AUC) similar to that in humans at the maximum recommended human dose (MRHD) of 5 mg.

Effect on Epithelial Tissues

Oral administration of risdiplam to rats and monkeys resulted in histopathological changes in epithelium of the gastrointestinal (GI) tract (apoptosis/single cell necrosis), lamina propria (vacuolation), the exocrine pancreas (single cell necrosis), the skin, tongue, and larynx (parakeratosis/hyperplasia/degeneration) with associated inflammation. The skin and GI epithelial effects were reversible. The no-effect doses for effects on epithelial tissues in rats and monkeys were associated with plasma exposures (AUC) similar to that in humans at the MRHD.

14 CLINICAL STUDIES

The efficacy of EVRYSDI for the treatment of patients with infantile-onset, later-onset, and pre-symptomatic SMA was evaluated in three clinical studies, Study 1 (NCT02913482) and Study 2 (NCT02908685), and Study 3 (NCT03779334), respectively.

The overall findings of these studies support the effectiveness of EVRYSDI in SMA pediatric and adult patients and appear to support the early initiation of treatment with EVRYSDI.

14.1 Infantile-Onset SMA

Study 1 was an open-label, 2-part study to investigate the efficacy, safety, pharmacokinetics, and pharmacodynamics of EVRYSDI for oral solution in patients with Type 1 SMA (symptom onset between 28 days and 3 months of age). All patients had genetic confirmation of homozygous deletion or compound heterozygosity predictive of loss of function of the SMN1 gene, and two SMN2 gene copies.

Part 1 of Study 1 was designed as a dose-finding study. Part 2 of Study 1 assessed the safety and efficacy of EVRYSDI at 0.20 mg/kg, the recommended dose determined in Part 1 [see Dosage and Administration (2.4)]. Patients from Part 1 did not take part in Part 2.

A total of 62 patients with symptomatic Type 1 SMA were enrolled in FIREFISH Part 1 (n = 21) and Part 2 (n = 41), of which 58 patients received the recommended dosage [see Dosage and Administration (2.1)]. The median age of onset of clinical signs and symptoms was 1.5 months (range: 0.9 to 3.0 months). The median age at enrollment was 5.6 months (range: 2.2 to 6.9 months), and the median time between onset of symptoms and the first dose was 3.7 months (range 1.0 to 6.0 months). Of these patients, 60% were female, 57% were Caucasian, and 29% were Asian. The demographics and baseline disease characteristics were comparable between Part 1 and Part 2 of the study.

Effectiveness was established based on the ability to sit without support for at least 5 seconds (as measured by Item 22 of the Bayley Scales of Infant and Toddler Development – Third Edition (BSID-III) gross motor scale) and on the basis of survival without permanent ventilation. Permanent ventilation was defined as requiring a tracheostomy or more than 21 consecutive days of either non-invasive ventilation (≥ 16 hours per day) or intubation, in the absence of an acute reversible event.

The primary endpoint was the proportion of patients with the ability to sit without support for at least 5 seconds (BSID-III gross motor scale, Item 22) after 12 months of treatment in Part 2; 29% of patients (n = 12/41) achieved this milestone.

Other efficacy endpoints of EVRYSDI-treated patients in Study 1 (pooled Part 1 and Part 2) are shown in Table 3.

Table 3 Key Efficacy Results at Month 12 and Month 24 (Study 1, Parts 1 and Part 2)
Efficacy Endpoints | Proportion of Patients Parts 1 & 2 at Month 12 | Proportion of Patients Parts 1 & 2 at Month 24
Motor Function and Development Milestones | N = 58 [Results were pooled from all patients who received the recommended dose of risdiplam (all patients in Part 2 and those in the high-dose cohort of Part 1; n = 58).]
BSID-III, Item 22: sitting without support for at least 5 seconds | 32.8% | 60.3%
Survival and Event-Free Survival | N = 62 [Results were pooled from all patients who received any dose of risdiplam in Part 1 and Part 2 (n = 62).]
Alive without Permanent Ventilation | 87.1% | 83.8%

At Month 24, 40% (23/58) of patients who received the recommended dose achieved sitting without support for 30 seconds (BSID-III, Item 26). In addition at Month 24, patients continued to achieve additional motor milestones; 28% (16/58) of patients achieved a standing measure (16% [9/58] supporting weight and 12% [7/58] standing with support), as measured by Section 2 of the Hammersmith Infant Neurological Examination (HINE-2) which assesses motor milestones.

The proportion of patients alive without permanent ventilation (event-free survival) was 84% for all patients at Month 24 (Table 3). Out of 62 patients, 6 infants died (4 within the first 3 months following study enrollment) and one additional patient withdrew from treatment and died 3.5 months later. Four patients required permanent ventilation by Month 24. These results indicate a clinically meaningful deviation from the natural history of untreated infantile-onset SMA. As described in the natural history of untreated infantile-onset SMA, patients would not be expected to attain the ability to sit independently, and no more than 25% of these patients would be expected to survive without permanent ventilation beyond 14 months of age.

14.2 Later-Onset SMA

Study 2 was a 2-part, multicenter trial to investigate the efficacy, safety, pharmacokinetics, and pharmacodynamics of EVRYSDI for oral solution in patients diagnosed with SMA Type 2 or Type 3. Part 1 of Study 2 was dose-finding and exploratory in 51 patients (14% ambulatory). Part 2 was randomized, double-blind, placebo-controlled, and is described below.

The primary endpoint in Study 2 Part 2 was the change from baseline to Month 12 in the Motor Function Measure 32 (MFM32) score. A key secondary endpoint was the proportion of patients with a 3-point or greater change from baseline to Month 12 in the MFM32 total score. The MFM32 measures motor function abilities that relate to daily functions. The total MFM32 score is expressed as a percentage (range: 0 to 100) of the maximum possible score, with higher scores indicating greater motor function. Another key secondary endpoint was the Revised Upper Limb Module (RULM). The RULM is a tool used to assess motor performance of the upper limb in SMA patients. It tests proximal and distal motor functions of the arm. The total score ranges from 0 (all the items cannot be performed) to 37 (all the activities are achieved fully without any compensatory maneuvers).

Study 2 Part 2 enrolled 180 non-ambulatory patients with Type 2 (71%) or Type 3 (29%) SMA. Patients were randomized 2:1 to receive EVRYSDI at the recommended dosage [see Dosage and Administration (2.1)] or placebo. Randomization was stratified by age group (2 to 5, 6 to 11, 12 to 17, or 18 to 25 years of age).

The median age of patients at the start of treatment was 9.0 years (range: 2 to 25), and the median time between onset of initial SMA symptoms and first treatment was 102.6 months (range: 1 to 275). Of the 180 patients included in the trial, 51% were female, 67% were Caucasian, and 19% were Asian. At baseline, 67% of patients had scoliosis (32% of them with severe scoliosis). Patients had a mean baseline MFM32 score of 46.1, and RULM score of 20.1. Overall baseline demographic characteristics were reasonably balanced between the treatment groups (EVRYSDI and placebo), with the exception of scoliosis (63% in the EVRYSDI arm vs. 73% in the placebo group).

The primary analysis on the change from baseline in MFM32 total score at Month 12 showed a clinically meaningful and statistically significant difference between patients treated with EVRYSDI and placebo. The results of the primary analysis and key secondary endpoints are shown in Table 4 and Figure 1.

Table 4 Summary of Efficacy in Patients with Later-Onset SMA at Month 12 of Treatment (Study 2 Part 2)
Endpoint | EVRYSDI (N = 120) | Placebo (N = 60)
Primary Endpoint:
Change from baseline in total MFM32 score at Month 12, LS means (95% CI) [The Mixed Model Repeated Measure (MMRM) analysis included the change from baseline total score as the dependent variable and as independent variables the baseline total score, treatment group, time, treatment-by-time interaction, and the randomization stratification variable of age group (2 to 5, 6 to 11, 12 to 17, 18 to 25).] , [The MFM total score was calculated according to the user manual, expressed as a percentage of the maximum score possible for the scale (i.e., sum of the 32 item scores divided by 96 and multiplied by 100).] , [Based on the missing data rule for MFM32, 6 patients were excluded from the analysis (EVRYSDI n = 115; placebo control n = 59).] | 1.36 (0.61, 2.11) | -0.19 (-1.22, 0.84)
Difference from Placebo, Estimate (95% CI) p-value | 1.55 (0.30, 2.81) 0.0156
Secondary Endpoints:
Proportion of patients with a change from baseline MFM32 total score of 3 or more at Month 12 (95% CI), | 38.3% (28.9, 47.6) | 23.7% (12.0, 35.4)
Odds ratio for overall response (95% CI) adjusted [The adjusted p-value was obtained for the endpoints included in the hierarchical testing and was derived based on all the p-values from endpoints in order of the hierarchy up to the current endpoint.] (unadjusted) p-value [The logistic regression analysis included the baseline total score, treatment and age group as independent variables.] | 2.35 (1.01, 5.44) 0.0469 (0.0469)
Change from baseline in total score of RULM at Month 12, LS means (95% CI), [Based on the missing data rule for RULM, 3 patients were excluded from the analysis (EVRYSDI n = 119; placebo control n = 58).] | 1.61 (1.00, 2.22) | 0.02 (-0.83, 0.87)
Difference from Placebo, Estimate (95% CI) adjusted (unadjusted) p-value | 1.59 (0.55, 2.62) 0.0469 (0.0028)

Figure 1 Mean Change from Baseline in Total MFM32 Score Over 12 Months (Study 2 Part 2) [Error bars denote the 95% confidence interval.] , [The MFM total score was calculated according to the user manual, expressed as a percentage of the maximum score possible for the scale (i.e., sum of the 32 item scores divided by 96 and multiplied by 100).]

14.3 Pre-Symptomatic SMA

Study 3 was an open-label, single-arm, multicenter clinical study to investigate the efficacy, safety, pharmacokinetics, and pharmacodynamics of EVRYSDI in infants up to 6 weeks of age (at first dose) who have been genetically diagnosed with SMA but do not yet present with symptoms.

The efficacy in pre-symptomatic SMA patients was evaluated at Month 12 in 26 patients treated with EVRYSDI in Study 3: 8 patients had 2 copies of the SMN2 gene, 13 patients had 3 copies, and 5 patients had 4 or more copies. The median age of these patients at first dose was 25 days (range: 16 to 41), 62% were female, and 85% were Caucasian. The primary efficacy population (N = 5) included patients with 2 SMN2 copies and a baseline CMAP amplitude ≥1.5 mV.

The primary efficacy endpoint was the proportion of patients with the ability to sit without support for at least 5 seconds (BSID-III gross motor scale, Item 22) at Month 12. This milestone was achieved by 80% (4/5) of patients in the primary efficacy population. This milestone was also achieved by 87.5% (7/8) of all patients with 2 copies of SMN2 and 96.2% (25/26) of patients in the full treated population.

At Month 12, 80.8% (21/26) of patients in the full treated population achieved sitting without support for 30 seconds (BSID-III, Item 26). Of the 26 patients treated with EVRYSDI, 25 patients had motor milestones measured by the HINE-2 at Month 12. Of these, 24 (96%) achieved sitting (23 patients could pivot/rotate and 1 achieved stable sit); 21 (84%) could stand (13 patients could stand unaided and 8 could stand with support); and 12 (48%) could walk independently. Seven patients were not tested for walking at Month 12. All 26 patients were alive at 12 months without permanent ventilation.

16 HOW SUPPLIED/STORAGE AND HANDLING

16.1 EVRYSDI for Oral Solution

How Supplied

Each amber glass bottle of EVRYSDI for oral solution is packaged with a bottle adapter, two 1 mL reusable oral syringes, two 6 mL reusable oral syringes, and one 12 mL reusable oral syringe. EVRYSDI for oral solution is a light yellow, pale yellow, yellow, greyish yellow, greenish yellow, or light green powder. Each bottle contains 60 mg of risdiplam (NDC 50242-175-07).

Storage and Handling

Store the dry powder at 20°C to 25°C (68°F to 77°F), excursions permitted between 15°C to 30°C (59°F to 86°F) [see USP controlled room temperature]. Keep in the original carton.

Keep the constituted oral solution of EVRYSDI in the original amber bottle to protect from light. Store in a refrigerator at 2°C to 8°C (36°F to 46°F) [see Dosage and Administration (2.4)].

16.2 EVRYSDI Tablets

How Supplied

Pale yellow film-coated tablet, round and curved, with EVR debossed on one side; available in HDPE bottles of 30 tablets with a child-resistant cap (NDC 50242-202-01).

Storage and Handling

Store at 20°C to 25°C (68°F to 77°F); excursions permitted between 15°C to 30°C (59°F to 86°F) [see USP Controlled Room Temperature]. Keep in the original bottle. Keep the bottle tightly closed in order to protect from moisture.

17 PATIENT COUNSELING INFORMATION

Advise the patient to read the FDA-approved patient labeling (Patient Information and Instructions for Use).

Pregnancy and Fetal Risk

Inform pregnant women and women of reproductive potential that, based on animal studies, EVRYSDI may cause fetal harm [see Use in Specific Populations (8.1)].

Discuss with women of childbearing age whether they are pregnant, might be pregnant, or are trying to become pregnant.

Advise women of childbearing potential to use effective contraception during treatment with EVRYSDI and for at least 1 month after stopping EVRYSDI.

Advise a female patient to immediately inform the prescriber if she is pregnant or planning to become pregnant [see Use in Specific Populations (8.3)].

Pregnancy Registry

Encourage patients to enroll in the EVRYSDI Pregnancy Registry if they become pregnant while taking EVRYSDI [see Use in Specific Populations (8.1)].

Potential Effects on Male Fertility

Advise male patients that their fertility may be compromised while on treatment with EVRYSDI [see Use in Specific Populations (8.3)].

Instructions for Preparation of Oral Solution

Advise patients/caregivers to ensure that EVRYSDI oral solution is in liquid form when received from the pharmacy.

Instruct patients/caregivers to take EVRYSDI oral solution with or without food or before or after breastfeeding at approximately the same time each day. However, instruct caregivers not to mix EVRYSDI with formula or milk.

Instruct patients/caregivers to take EVRYSDI oral solution immediately after it is drawn up into the reusable oral syringe [see Dosage and Administration (2.2)].

Instructions for EVRYSDI Tablets

Advise patients/caregivers to swallow EVRYSDI tablets whole with water. Do not chew, cut, or crush the tablets.

Alternatively, the tablet can be dispersed in one teaspoon (5 mL) of room temperature non-chlorinated drinking water (e.g., filtered water) and taken immediately. EVRYSDI tablets must not be dispersed in any liquid other than non-chlorinated drinking water. Instruct the patient/caregivers that the dispersion must be administered within 10 minutes of adding non-chlorinated drinking water, or it must be discarded [see Dosage and Administration (2.2)].

Advise patients/caregivers to wash their hands before and after preparing or taking EVRYSDI tablets.

Advise patients/caregivers to avoid getting the dispersed tablet on their skin or in their eyes. Advise patients/caregivers to wash the area with soap and water if the dispersed tablet gets on the skin. Advise patients/caregivers to rinse their eyes with water if the dispersed tablet gets in the eyes.

Advise patients/caregivers to use a dry paper towel to dry the area if the dispersion is spilled and then clean with soap and water. Advise patients/caregivers to throw the paper towel away in the trash and wash their hands with soap and water.

EVRYSDI® [risdiplam]

Distributed by:
Genentech USA, Inc.
A Member of the Roche Group
1 DNA Way
South San Francisco, CA 94080-4990

EVRYSDI is a registered trademark of Genentech, Inc.
©2026 Genentech, Inc. All rights reserved.

Patient Information

EVRYSDI® [ev-RIZ-dee]
(risdiplam)
for oral solution

EVRYSDI® [ev-RIZ-dee]
(risdiplam)
tablets, for oral use

What is EVRYSDI?

- EVRYSDI is a prescription medicine used to treat spinal muscular atrophy (SMA) in children and adults.

Before taking EVRYSDI, tell your healthcare provider about all of your medical conditions, including if you:

- are pregnant or plan to become pregnant. If you are pregnant, or are planning to become pregnant, ask your healthcare provider for advice before taking this medicine. EVRYSDI may harm your unborn baby.
- are a woman who can become pregnant:
  - Before you start your treatment with EVRYSDI, your healthcare provider may test you for pregnancy. Because EVRYSDI may harm your unborn baby, you and your healthcare provider will decide if taking EVRYSDI is right for you during this time.
  - Talk to your healthcare provider about birth control methods that may be right for you. Use birth control while on treatment and for at least 1 month after stopping EVRYSDI.
  - Pregnancy Registry. There is a pregnancy registry for women who take EVRYSDI during pregnancy. The purpose of this registry is to collect information about the health of the pregnant woman and her baby. If you are pregnant or become pregnant while receiving EVRYSDI, tell your healthcare provider right away. Talk to your healthcare provider about registering with the EVRYSDI Pregnancy Registry. Your healthcare provider can enroll you in this registry or you can enroll by calling 1-833-760-1098 or visiting https://www.evrysdipregnancyregistry.com.
- are an adult male planning to have children: EVRYSDI may affect a man's ability to have children (fertility). If this is of concern to you, make sure to ask a healthcare provider for advice.
- are breastfeeding or plan to breastfeed. It is not known if EVRYSDI passes into breast milk and may harm your baby. If you plan to breastfeed, discuss with your healthcare provider about the best way to feed your baby while on treatment with EVRYSDI.

Tell your healthcare provider about all the medicines you take, including prescription and over-the-counter medicines, vitamins, and herbal supplements. Keep a list of them to show your healthcare provider, including your pharmacist, when you get a new medicine.

How should I take EVRYSDI?

- For infants and children, your healthcare provider will determine the daily dose of EVRYSDI needed based on your child's age and weight. For adults, take 5 mg of EVRYSDI daily.
- Your healthcare provider will either prescribe:
  EVRYSDI for oral solution
  Or
  EVRYSDI tablet
- Your healthcare provider will tell you how long you or your child needs to take EVRYSDI. Do not stop treatment with EVRYSDI unless your healthcare provider tells you to.
  - Take EVRYSDI exactly as your healthcare provider tells you to take it. Do not change the dose without talking to your healthcare provider.
- Avoid getting EVRYSDI on your skin or in your eyes. If it gets on your skin, wash the area with soap and water. If it gets in your eyes, rinse your eyes with water.

If you are taking EVRYSDI for oral solution:

- See the detailed Instructions for Use that comes with it for information on how to take or give EVRYSDI for oral solution.
- You should receive EVRYSDI from the pharmacy as a liquid that can be given by mouth or through a feeding tube. The liquid solution is prepared by your pharmacist or other healthcare provider. If the medicine in the bottle is a powder, do not use it. Contact your pharmacist for a replacement.
- Take EVRYSDI one time daily with or without a meal at about the same time each day. Drink water afterwards to make sure EVRYSDI has been completely swallowed.
- In infants who are breastfed, EVRYSDI can be given before or after breastfeeding.
- Do not mix EVRYSDI with formula or milk.
- If you are unable to swallow and have a nasogastric (NG-tube) or gastrostomy tube (G-tube), EVRYSDI for oral solution can be given through the tube.

Reusable Oral Syringes for EVRYSDI for Oral Solution

- Your pharmacist will provide you with the reusable oral syringes that are needed for taking your medicine and explain how to use them. You should receive 1 or 2 identical oral syringes depending on your prescribed daily dose.
- From the bottle, draw up (measure) the dose of EVRYSDI with these syringes, as they are made to protect the medicine from light.
- Take EVRYSDI right away after it has been drawn into the syringe. Do not store the EVRYSDI solution in the syringe. If EVRYSDI is not taken within 5 minutes of when it is drawn up, throw away the solution by pressing the plunger and prepare a new dose with the same syringe.
- Do not throw the syringes away because they are reusable.
- Wash the syringes per instructions after use.
- Contact your healthcare provider or pharmacist if your oral syringes are lost or damaged.

If you are taking EVRYSDI Tablets:

- See the detailed Instructions for Use that comes with it for information on how to take or give EVRYSDI tablets.
- Wash your hands before and after preparing or taking EVRYSDI tablets.
- Take EVRYSDI one time daily with or without a meal at about the same time each day.
- Do not chew, cut, or crush the tablet.
- Swallow the EVRYSDI tablet whole with some water.
- If you cannot swallow tablets whole or if you have a nasogastric (NG-tube) or gastrostomy (G-tube), see the detailed Instructions for Use that comes with it for information on how to take or give EVRYSDI tablets.

If you miss a dose of EVRYSDI:

- If you remember the missed dose within 6 hours of when you normally take EVRYSDI, then take the dose. Continue taking EVRYSDI at your usual time the next day.
- If you remember the missed dose more than 6 hours after you normally take EVRYSDI, skip the missed dose. Take your next dose at your usual time the next day.
- If you do not fully swallow the dose, or you vomit after taking a dose, do not take another dose of EVRYSDI to make up for that dose. Wait until the next day to take the next dose at your usual time.

What are the possible side effects of EVRYSDI?
The most common side effects of EVRYSDI include:

- For later-onset SMA:

- fever

- diarrhea

- rash

- For infantile-onset SMA:

- fever
- diarrhea
- rash

- runny nose, sneezing, and sore throat (upper respiratory infection)
- lung infection (lower respiratory infection)

- constipation
- vomiting
- cough

These are not all of the possible side effects of EVRYSDI. For more information, ask your healthcare provider or pharmacist.
Call your doctor for medical advice about side effects. You may report side effects to FDA at 1-800-FDA-1088.

How should I store EVRYSDI?
EVRYSDI for Oral Solution:

- Store EVRYSDI in the refrigerator between 36°F to 46°F (2°C to 8°C). Do not freeze.
  - If necessary, EVRYSDI can be kept at room temperature up to 104°F (up to 40°C) for a combined total of 5 days. EVRYSDI can be removed from, and returned to, a refrigerator. The total combined time out of refrigeration should not be more than 5 days.
- Keep EVRYSDI in an upright position in the original amber bottle to protect from light.
- Throw away (discard) any unused portion of EVRYSDI 64 days after it is mixed by the pharmacist (constitution) or if EVRYSDI has been kept at room temperature (below 104°F [40°C]) for more than a total combined time of 5 days. Discard EVRYSDI if it has been kept above 104°F (40°C). Please see the Discard After date written on the bottle label. (See the Instructions for Use that comes with EVRYSDI for oral solution).

EVRYSDI Tablets:

- Store at room temperature between 68°F to 77°F (20°C to 25°C).
- Keep the tablets in their original bottle with the cap tightly closed to protect from moisture.

Keep EVRYSDI, all medicines and syringes out of the reach of children.

General information about the safe and effective use of EVRYSDI.
Medicines are sometimes prescribed for purposes other than those listed in a Patient Information leaflet. Do not use EVRYSDI for a condition for which it was not prescribed. Do not give EVRYSDI to other people, even if they have the same symptoms you have. It may harm them. You can ask your pharmacist or healthcare provider for information about EVRYSDI that is written for health professionals.

What are the ingredients in EVRYSDI?
Active ingredient: risdiplam
Inactive ingredients:
EVRYSDI for Oral Solution: ascorbic acid, disodium edetate dihydrate, isomalt, mannitol, polyethylene glycol 6000, sodium benzoate, strawberry flavor, sucralose, and tartaric acid.
EVRYSDI Tablets: colloidal silicon dioxide, crospovidone, mannitol, microcrystalline cellulose, polyethylene glycol 3350, polyvinyl alcohol, sodium stearyl fumarate, strawberry flavor, talc, tartaric acid, titanium dioxide, and yellow iron oxide.
Distributed by: Genentech USA, Inc., A Member of the Roche Group, 1 DNA Way, South San Francisco, CA 94080-4990
EVRYSDI is a registered trademark of Genentech, Inc.
©2026 Genentech, Inc. All rights reserved.
For more information, go to www.EVRYSDI.com or call 1-833-387-9734.

This Patient Information has been approved by the U.S. Food and Drug Administration.

Issued: 2/2026

INSTRUCTIONS FOR USE
EVRYSDI® [ev-RIZ-dee]
(risdiplam)
for oral solution

Please read and understand this Instructions for Use and the Patient Information leaflet before you start taking EVRYSDI for information about EVRYSDI and how to prepare and give EVRYSDI through an oral syringe, gastrostomy tube (G-tube), or nasogastric tube (NG-tube).

If you have any questions about how to take EVRYSDI, contact your healthcare provider.

EVRYSDI should come as a liquid in a bottle when you receive it from the pharmacy. Do not take EVRYSDI and contact your pharmacist if the medicine in the bottle is a powder.

Each EVRYSDI carton contains (see Figure A):

1 Cap

Figure A

1 Bottle adapter

1 EVRYSDI bottle

1 or 2 Reusable oral syringe(s)

1 Instructions for Use (not shown)

1 Prescribing Information and Patient Information (not shown)

Reusable Oral Syringe Overview (see Figure B)

Figure B

Important information about EVRYSDI

- Ask your healthcare provider to show you the correct oral syringe you should use and how to measure your prescribed daily dose.
- Always use the reusable oral syringes that come with EVRYSDI to measure your prescribed daily dose. If your carton does not contain two identical syringes, contact your pharmacist.
- Always take EVRYSDI exactly as your healthcare provider tells you to take it.
- Take EVRYSDI 1 time daily with or without a meal at approximately the same time each day.
- Do not take EVRYSDI if the bottle adapter is not in the bottle. If the bottle adapter is not in the bottle, contact your pharmacist.
- Do not mix EVRYSDI into food or liquids. Do not mix EVRYSDI with formula or milk.
- Do not take EVRYSDI if the bottle or oral syringes are damaged.
- Avoid getting EVRYSDI on your skin or in your eyes. If EVRYSDI gets on your skin, wash the area with soap and water. If EVRYSDI gets in your eyes, rinse your eyes with water.
- If you spill EVRYSDI, dry the area with a dry paper towel and then clean with water. Throw away the paper towel in the trash and wash your hands well with soap and water.
- If there is not enough EVRYSDI left in the bottle for your prescribed dose, throw away (discard) the bottle with remaining EVRYSDI and used oral syringes according to your local requirements.
- Use a new bottle of EVRYSDI to get your prescribed dose.
  Do not mix EVRYSDI from the new bottle with the bottle you are currently using.

How to store EVRYSDI

- Store EVRYSDI in the refrigerator between 36°F to 46°F (2°C to 8°C). Do not freeze.
- If necessary, EVRYSDI can be kept at room temperature up to 104°F (up to 40°C) for a combined total of 5 days. EVRYSDI can be removed from, and returned to, a refrigerator. The total combined time out of refrigeration should not be more than 5 days. Throw away EVRYSDI if it has been kept at room temperature for more than 5 days.
- Store EVRYSDI in the original amber bottle in an upright position with the cap tightly closed.
- Throw away (discard) any unused portion of EVRYSDI 64 days after mixed by the pharmacist (constitution) when stored in the refrigerator at 36°F to 46°F (2°C to 8°C). Please see the Discard After date written on the bottle label (see Figure C).
- Ask your pharmacist for the Discard After date if it is not written on the bottle label.
- Throw away any unused portion of EVRYSDI that has been kept above 104°F (40°C).
- Keep EVRYSDI, all medicines and syringes out of the reach of children.

Figure C

A) Preparing and withdrawing your dose

How to prepare your dose of EVRYSDI

Figure D

Step A1
Remove the cap by pushing it down and then twisting the cap to the left (counterclockwise) (See Figure D).
Do not throw away the cap.

Figure E

Step A2
Push the plunger of the oral syringe all the way down to remove any air in the oral syringe (See Figure E).

Figure F

Step A3
Place the EVRYSDI bottle on a flat surface. While keeping the bottle in an upright position, insert the syringe tip into the bottle adapter (See Figure F).

Figure G

Step A4
Carefully turn the bottle upside down with the syringe tip firmly inserted into the bottle adapter (See Figure G).

Figure H

Step A5
Slowly pull back on the plunger to withdraw your prescribed dose of EVRYSDI.
The top of the black plunger stopper must line up with the mL marking on the oral syringe for your prescribed daily dose (See Figure H).
After the correct dose is withdrawn, hold the plunger in place to keep the plunger from moving.

Figure I

Step A6
Continue to hold the plunger in place to keep the plunger from moving. Leave the oral syringe in the bottle adapter and turn the bottle to an upright position. Place the bottle onto a flat surface. Remove the oral syringe from the bottle adapter by gently pulling straight up on the oral syringe while holding the plunger in place (See Figure I).

Figure J

Step A7
Hold the oral syringe with the syringe tip pointing up. Check the EVRYSDI in the oral syringe. If there are large air bubbles in the oral syringe (See Figure J) or if you have drawn up the wrong dose of EVRYSDI, insert the syringe tip firmly into the bottle adapter while the bottle is in an upright position. Push the plunger all the way down so that EVRYSDI flows back into the bottle and repeat Steps A4 through A7.
Take or give EVRYSDI right away after it is drawn up into the oral syringe. If it is not taken within 5 minutes, throw away EVRYSDI liquid from your oral syringe into the household trash. Do this by pushing the plunger all the way down to remove EVRYSDI from the oral syringe. Prepare a new dose starting with Step A2.

Figure K

Step A8
Put the cap back on the bottle. Turn the cap to the right (clockwise) to tightly close the bottle (See Figure K). Do not remove the bottle adapter from the bottle.

If you are taking your dose of EVRYSDI by mouth, follow the instructions in "B) How to take a dose of EVRYSDI by mouth".

If you are taking your dose of EVRYSDI through a gastrostomy tube, follow the instructions in "C) How to give a dose of EVRYSDI through a gastrostomy tube".

If you are taking your dose of EVRYSDI through a nasogastric tube, follow the instructions in "D) How to give a dose of EVRYSDI through a nasogastric tube".

B) How to take a dose of EVRYSDI by mouth

Sit upright when taking a dose of EVRYSDI by mouth.

Figure L

Step B1
Place the oral syringe into the mouth with the tip along either cheek.
Slowly push the plunger all the way down to give the full dose of EVRYSDI (See Figure L).
Giving EVRYSDI into the throat or too fast may cause choking.

Figure M

Step B2
Check that there is no EVRYSDI left in the oral syringe (See Figure M).

Figure N

Step B3
Drink about a tablespoon (15 mL) of water right after taking the prescribed dose of EVRYSDI to make sure the drug has been completely swallowed (See Figure N).
Go to Step E for cleaning of the syringe.

C) How to give a dose of EVRYSDI through a gastrostomy tube

If you are giving EVRYSDI through a gastrostomy tube, ask your healthcare provider to show you how to inspect the gastrostomy tube before giving EVRYSDI.

Figure O

Step C1
Place the oral syringe tip into the gastrostomy tube. Slowly push the plunger all the way down to give the full dose of EVRYSDI (See Figure O).

Figure P

Step C2
Check that there is no EVRYSDI left in the oral syringe (See Figure P).

Figure Q

Step C3
Flush the gastrostomy tube with 10 mL to 20 mL of water right after giving the prescribed dose of EVRYSDI (See Figure Q).
Go to Step E for cleaning of the syringe.

D) How to give a dose of EVRYSDI through a nasogastric tube

If you are giving EVRYSDI through a nasogastric tube, ask your healthcare provider to show you how to inspect the nasogastric tube before giving EVRYSDI.

Figure R

Step D1
Place the oral syringe tip into the nasogastric tube. Slowly press the plunger all the way down to give the full dose of EVRYSDI (See Figure R).

Figure S

Step D2
Check that there is no EVRYSDI left in the oral syringe (See Figure S).

Figure T

Step D3
Flush the nasogastric tube with 10 mL to 20 mL of water right after giving the prescribed dose of EVRYSDI (See Figure T).
Go to Step E for cleaning of the syringe.

E) How to clean the oral syringe after use

Figure U

Step E1
Remove the plunger from the oral syringe by pulling the plunger away from the syringe until the plunger comes out of the syringe.
Rinse the oral syringe barrel well under clean water (See Figure U).

Figure V

Step E2
Rinse the plunger well under clean water (See Figure V).

Figure W

Step E3
Check that the oral syringe barrel and plunger are clean.
Place the oral syringe barrel and plunger on a clean surface in a safe place to dry (See Figure W).
Wash your hands with soap and water.
After the oral syringe barrel and plunger are dry, put the plunger back into the oral syringe barrel and store the syringe with your medicine.

EVRYSDI is a registered trademark of Genentech, Inc.

Distributed by:
Genentech, Inc.
1 DNA Way
South San Francisco, CA 94080-4990
Approved: 2/2025
This Instructions for Use has been Approved by the U.S. Food and Drug Administration.

©2025 Genentech, Inc. All Rights Reserved

EVRYSDI®
(risdiplam) for oral solution

Instructions for Constitution
(FOR HEALTHCARE PROVIDERS ONLY)

Each EVRYSDI carton contains (see Figure A):

1 Cap

Figure A

1 EVRYSDI bottle

1 Reusable oral syringe 12 mL

2 Reusable oral syringes 6 mL

2 Reusable oral syringes 1 mL

1 Press-in bottle adapter

1 Prescribing Information (not shown)

1 Instructions for Constitution (not shown)

1 Instructions for Use (not shown)

Important information about EVRYSDI

- Do not use if the powder expiration date has passed. The powder expiration date is printed on the bottle label.
- Do not use the medicine if any of the supplies are damaged or missing.
- Use purified water to constitute the medicine.
- Select the appropriate oral syringes (1 mL, 6 mL, or 12 mL) based on the patient's dose and provide instruction to the patient/caregiver on how to administer their dose. The oral syringes provided in the carton are intended to be reusable.
- Only use the amber oral syringe provided for use with EVRYSDI. Other syringes may not be compatible with the press-in-bottle adapter and may not protect the product from light.

How to store EVRYSDI

- Store the dry powder at 20°C to 25°C (68°F to 77°F), excursions permitted between 15°C to 30°C (59°F to 86°F) [see USP controlled room temperature]. Keep in the original carton.
- Store the constituted oral solution of EVRYSDI upright in the original amber bottle in a refrigerator at 2°C to 8°C (36°F to 46°F). Do not freeze.

Important precautions for preparation of EVRYSDI

- Avoid inhalation and direct contact with skin or mucous membranes with the dry powder and the constituted solution. If such contact occurs, wash thoroughly with soap and water; rinse eyes with water.
- Wear disposable gloves during the preparation and clean up procedure.

Constitution

Figure B

Step 1
Gently tap the bottom of the bottle to loosen the powder (See Figure B).

Figure C

Step 2
Remove the cap by pushing it down and then twisting to the left (counter-clockwise) (See Figure C). Do not throw away the cap.

Figure D

Step 3
Carefully pour 79 mL of purified water into the medicine bottle (See Figure D).

Figure E

Step 4
Hold the medicine bottle on a table with one hand.
Insert the press-in bottle adapter into the opening by pushing it down with the other hand. Ensure it is completely pressed against the bottle lip (See Figure E).

Figure F

Step 5
Put the cap back on the bottle. Turn the cap to the right (clockwise) to close the bottle.
Ensure it is completely closed and then shake well for 15 seconds (See Figure F).
Wait for 10 minutes. You should have obtained a clear solution.
If not, shake well again for another 15 seconds or until you have obtained a clear solution.

Figure G

Step 6
Calculate the Discard After date of the oral solution as 64 days after constitution (Note: The day of constitution is counted as day 0. For example, if constitution is on the 1st of April, the Discard After date will be the 4th of June).
Write the Discard After date of the solution and the Lot number on the bottle label (See Figure G).
Do not dispense the constituted solution if the solution's Discard After date exceeds the original powder expiration date.

Figure H

Step 7
Remove and discard the peel-off part of the bottle label with the expiration date of the powder (See Figure H).

Selecting the oral syringe for the prescribed daily dose of EVRYSDI

For the calculation of dosing volume, the syringe increments need to be considered. Round the dose volume to the closest increment marked on the selected oral syringe.

Select the correct oral syringe(s) (1 mL, 6 mL, or 12 mL) for the calculated dosing volume according to the table below and remove the other oral syringes.

Dose Strength | Syringe Size | Dosing Volume | Syringe Increments
0.75 mg/mL | 1 mL | 0.3 mL to 1 mL | 0.01 mL
0.75 mg/mL | 6 mL | 1 mL to 6 mL | 0.1 mL
0.75 mg/mL | 12 mL | 6.2 mL to 6.6 mL | 0.2 mL

Put the bottle back in its original carton with the correct oral syringes, Prescribing Information, and Instructions for Use.

Store the constituted oral solution of EVRYSDI upright in the original amber bottle in a refrigerator at 2°C to 8°C (36°F to 46°F). Do not freeze. Discard any unused portion 64 days after constitution.

EVRYSDI is a registered trademark of Genentech, Inc.

Distributed by:
Genentech, Inc.
1 DNA Way
South San Francisco, CA 94080-4990
Revision Date: 2/2025
©2025 Genentech, Inc. All Rights Reserved.

Representative sample of labeling (see the HOW SUPPLIED section for complete listing):

INSTRUCTIONS FOR USE

EVRYSDI® [ev-RIZ-dee]
(risdiplam)
Tablets, for oral use

Before you start

This Instructions for Use contains information on how to prepare and take EVRYSDI tablets.

Read this Instructions for Use and Patient Information leaflet before you start taking or giving EVRYSDI tablets for the first time and each time you get a refill. There may be new information. This information does not take the place of talking with your healthcare provider about your medical condition or treatment.

If you have any questions about how to take EVRYSDI, contact your healthcare provider.

Important Information

- If you are taking EVRYSDI tablets, the daily dose is one tablet.
- EVRYSDI tablets can be swallowed whole with water. Do not chew, cut, or crush the tablet.
- If you are unable to swallow EVRYSDI tablets whole or have a nasogastric (NG) tube or gastrostomy tube (G-tube), your healthcare provider will show you how to prepare and take EVRYSDI tablets. Always take EVRYSDI tablets exactly as your healthcare provider tells you.
- Do not take or give EVRYSDI tablets until you have been shown the right way to prepare and take or give EVRYSDI.
- Wash your hands before and after preparing, taking or giving EVRYSDI.
- Check the expiration date and check the product for damage before use. Do not use if expired or damaged.
- Avoid getting the EVRYSDI tablet mixture on your skin or in your eyes. If the EVRYSDI tablet mixture gets on your skin, wash the area with soap and water. If the tablet mixture gets in your eyes, rinse your eyes with water.
- Keep the EVRYSDI tablet mixture out of sunlight.
- If you spill the EVRYSDI tablet mixture, dry the area with a dry paper towel and then clean with soap and water. Throw away the paper towel in the trash and wash your hands with soap and water.
- Do not take an extra dose if you vomit at any time after taking EVRYSDI.

How to store EVRYSDI tablets

- Store EVRYSDI tablets at room temperature between 68°F to 77°F (20°C to 25°C)
- Do not take or give EVRYSDI if it has been exposed to temperatures above 86°F (30°C).
- Keep tablets in the original bottle. Keep the bottle tightly closed to protect from moisture.
- Keep EVRYSDI and all medicines out of the sight and reach of children.

If able to swallow the EVRYSDI tablet whole:

Swallow the tablet whole with water.

Do not chew, cut, or crush the tablet.

Do not swallow with any liquids other than water.

Wash your hands with soap and water

If unable to swallow the EVRYSDI tablet whole:
Prepare an EVRYSDI tablet mixture

Gather supplies
(Figure A):

- 1 EVRYSDI tablet
- a small, clean empty cup
- 1 teaspoon (5 mL) of room temperature non-chlorinated drinking water (such as filtered water) for mixing
- at least 1 tablespoon (15 mL) of non-chlorinated drinking water (such as filtered water) for rinsing
- If giving EVRYSDI through a feeding tube: 1 dosing syringe that connects to the feeding tube

Figure A

The cup and the dosing syringe are not included in the package. Obtain a dosing syringe from your healthcare provider or pharmacist. Your healthcare provider or pharmacist can help you choose the right dosing syringe.

Step 1. Wash your hands with soap and water (Figure B).

Figure B

Step 2. Remove the cap by pushing down and then twisting the child resistant cap to the left (counterclockwise) (Figure C).

Figure C

Step 3. Take 1 tablet out of the bottle (Figure D).

Figure D

Step 4. Replace the child resistant cap on the bottle, turn the cap to the right (clockwise) until tightly closed. (Figure E).
Do not store EVRYSDI outside the original container due to moisture sensitivity.

Figure E

Step 5
Put 1 teaspoon (5 mL) of room temperature non-chlorinated drinking water (such as filtered water) in a small cup and add 1 tablet.

- Do not use any liquids other than non-chlorinated drinking water (such as filtered water).
- Do not expose the mixture to sunlight.

Figure F

Step 6
Gently swirl the cup until it is fully mixed. Some particles may remain after swirling. This may take up to 3 minutes. (Figure F).

Option A: To take or give the tablet mixture by mouth, see Step A1
Option B: To take or give the tablet mixture by feeding tube, see Step B1

Option A: Take or give EVRYSDI tablet mixture by mouth

Step A1
Drink or give the tablet mixture right away. Throw away the mixture if not used within 10 minutes of adding the tablet to the cup with non-chlorinated drinking water (such as filtered water) (Figure G).

Figure G

Step A2
Refill the cup with at least 1 tablespoon (15 mL) of non-chlorinated drinking water (such as filtered water) and swirl to get any medicine left in the cup (Figure H).

Figure H

Step A3
Drink the 2nd mixture right away. (Figure I).

Figure I

Step A4
Wash your hands and all the items used to give EVRYSDI (Figure J).

Figure J

Option B: Take or give EVRYSDI tablet mixture through a feeding tube (gastrostomy or nasogastric tube)

You can take or give the EVRYSDI tablet mixture through a feeding tube (gastrostomy or nasogastric tube) placed by a healthcare provider.
Check the manufacturer's instructions for the size and dimensions of the gastrostomy or nasogastric tube.
Make sure that the gastrostomy or nasogastric tube size is at least 8 French or higher to prevent clogging of the feeding tube. Ask your healthcare provider to show you how to check the feeding tube before giving EVRYSDI.

Step B1
Take or give EVRYSDI tablet mixture right away. Throw away the mixture if not used within 10 minutes of adding the tablet to the cup with non-chlorinated drinking water (such as filtered water).
Place the dosing syringe tip into the cup and slowly pull up the plunger to draw up all the mixture (Figure K).

Figure K

Step B2
Place the dosing syringe tip into the gastrostomy or nasogastric tube. Slowly push the plunger all the way down to give the full dose of EVRYSDI (Figure L1 or L2).

Figure L1
(gastrostomy tube)

Figure L2
(nasogastric tube)

Step B3
Check that there is no EVRYSDI left in the dosing syringe (Figure M).

Figure M

Step B4
Refill the cup with at least 1 tablespoon (15 mL) of non-chlorinated drinking water (such as filtered water) and swirl to get any medicine left in the cup (Figure N).
Place the dosing syringe into the cup and pull up the plunger to draw up all the mixture.

Figure N

Step B5
Flush the gastrostomy or nasogastric tube with the mixture (Figure O1 or O2).

Figure O1
(gastrostomy tube)

Figure O2
(nasogastric tube)

Step B6
Wash your hands and all the items used to give EVRYSDI (Figure P).
Check with your pharmacist if the dosing syringe provided is for single use only or can be re-used multiple times. Follow the manufacturer's instructions to throw away or immediately clean your dosing syringe.

Figure P

Distributed by:
Genentech, USA Inc., A Member of the Roche Group
1 DNA Way, South San Francisco, CA 94080-4990

Evrysdi® is a registered trademark of Genentech, Inc.
©2026 Genentech, Inc.

This Instructions for Use has been approved by the U.S. Food and Drug Administration.

Approved: 2/2026

PRINCIPAL DISPLAY PANEL - 60 mg/80 mL Bottle Carton

NDC 50242-175-07

Evrysdi®
(risdiplam)
for oral solution

60 mg/80 mL
(0.75 mg/mL)

Attention pharmacist: Evrysdi must be
constituted with water prior to dispensing.

80 mL (2.71 fl oz) total volume after constitution

Rx only

Genentech

11044976

PRINCIPAL DISPLAY PANEL - 5 mg Tablet Bottle Carton

NDC 50242-202-01

Evrysdi®
(risdiplam)
Tablets

5 mg

Do not chew, cut,
or crush tablet.

30 Tablets

Rx only

Genentech

11044980